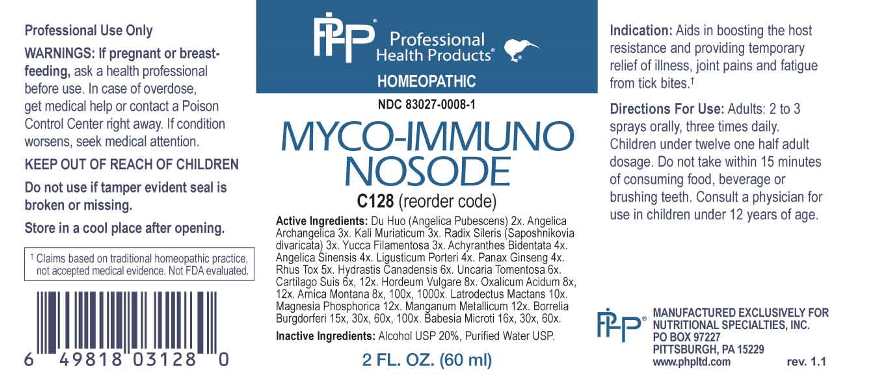 DRUG LABEL: Myco Immuno Nosode
NDC: 83027-0008 | Form: SPRAY
Manufacturer: Nutritional Specialties, Inc.
Category: homeopathic | Type: HUMAN OTC DRUG LABEL
Date: 20230317

ACTIVE INGREDIENTS: ANGELICA PUBESCENS ROOT 2 [hp_X]/1 mL; ANGELICA ARCHANGELICA ROOT 3 [hp_X]/1 mL; POTASSIUM CHLORIDE 3 [hp_X]/1 mL; SAPOSHNIKOVIA DIVARICATA ROOT 3 [hp_X]/1 mL; YUCCA FILAMENTOSA WHOLE 3 [hp_X]/1 mL; ACHYRANTHES BIDENTATA ROOT 4 [hp_X]/1 mL; ANGELICA SINENSIS ROOT 4 [hp_X]/1 mL; LIGUSTICUM PORTERI ROOT 4 [hp_X]/1 mL; ASIAN GINSENG 4 [hp_X]/1 mL; TOXICODENDRON PUBESCENS LEAF 5 [hp_X]/1 mL; GOLDENSEAL 6 [hp_X]/1 mL; UNCARIA TOMENTOSA ROOT 6 [hp_X]/1 mL; SUS SCROFA CARTILAGE 6 [hp_X]/1 mL; BARLEY 8 [hp_X]/1 mL; OXALIC ACID DIHYDRATE 8 [hp_X]/1 mL; ARNICA MONTANA WHOLE 8 [hp_X]/1 mL; LATRODECTUS MACTANS 10 [hp_X]/1 mL; MAGNESIUM PHOSPHATE, DIBASIC TRIHYDRATE 12 [hp_X]/1 mL; MANGANESE 12 [hp_X]/1 mL; BORRELIA BURGDORFERI 15 [hp_X]/1 mL; BABESIA MICROTI 16 [hp_X]/1 mL
INACTIVE INGREDIENTS: WATER; ALCOHOL

DRUG FACTS:

ACTIVE INGREDIENTS:

Du Huo (Angelica Pubescens) 2X, Angelica Archangelica 3X, Kali Muriaticum 3X, Radix Sileris (Saposhnikovia Divaricata) 3X, Yucca Filamentosa 3X, Achyranthes Bidentata 4X, Angelica Sinensis 4X, Ligusticum Porteri 4X, Panax Ginseng 4X, Rhus Tox 5X, Hydrastis Canadensis 6X, Uncaria Tomentosa 6X, Cartilago Suis 6X, 12X, Hordeum Vulgare 8X, Oxalicum Acidum 8X, 12X, Arnica Montana 8X, 100X, 1000X, Latrodectus Mactans 10X, Magnesia Phosphorica 12X, Manganum Metallicum 12X, Borrelia Burgdorferi 15X, 30X, 60X, 100X, Babesia Microti 16X, 30X, 60X.

PURPOSE:

Aids in boosting the host resistance and providing temporary relief of illness, joint pains and fatigue from tick bites.†

†Claims based on traditional homeopathic practice, not accepted medical evidence. Not FDA evaluated.

WARNINGS:

Professional Use Only

If pregnant or breast-feeding, ask a health professional before use.

In case of overdose, get medical help or contact a Poison Control Center right away.

If condition worsens, seek medical attention.

KEEP OUT OF REACH OF CHILDREN

Do not use if tamper evident seal is broken or missing.

Store in a cool place after opening

KEEP OUT OF REACH OF CHILDREN:

In case of overdose, get medical help or contact a Poison Control Center right away.

DIRECTIONS:

Adults: 2 to 3 sprays orally, three times daily. Children under twelve one half adult dosage. Do not take within 15 minutes of consuming food, beverage or brushing teeth. Consult a physician for use in children under 12 years of age.

INDICATIONS:

Aids in boosting the host resistance and providing temporary relief of illness, joint pains and fatigue from tick bites.†

†Claims based on traditional homeopathic practice, not accepted medical evidence. Not FDA evaluated.

INACTIVE INGREDIENTS:

Alcohol USP 20%, Purified Water USP.

QUESTIONS:

MANUFACTURED EXCLUSIVELY FOR

NUTRITIONAL SPECIALTIES, INC.

PO BOX 97227

PITTSBURG, PA 15229

www.phpltd.com

PACKAGE LABEL DISPLAY:

Professional

Health Products

HOMEOPATHIC

NDC 83027-0008-1

MYCO-IMMUNO

NOSODE

2 FL. OZ (60 ml)